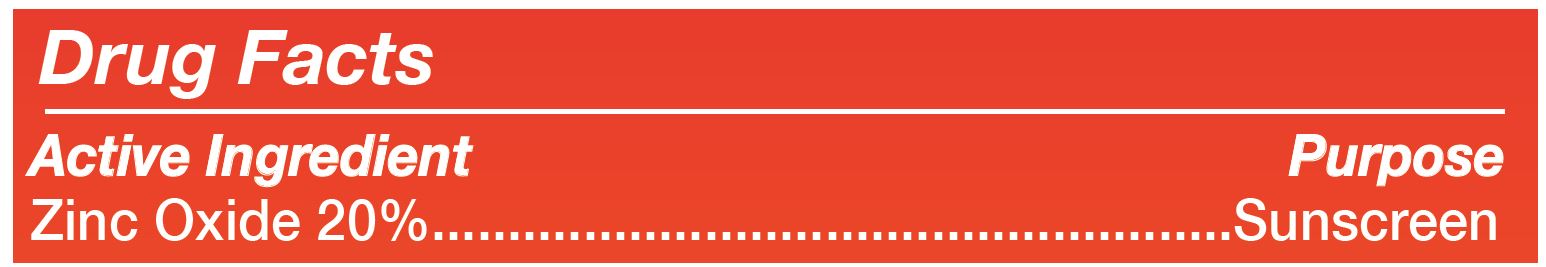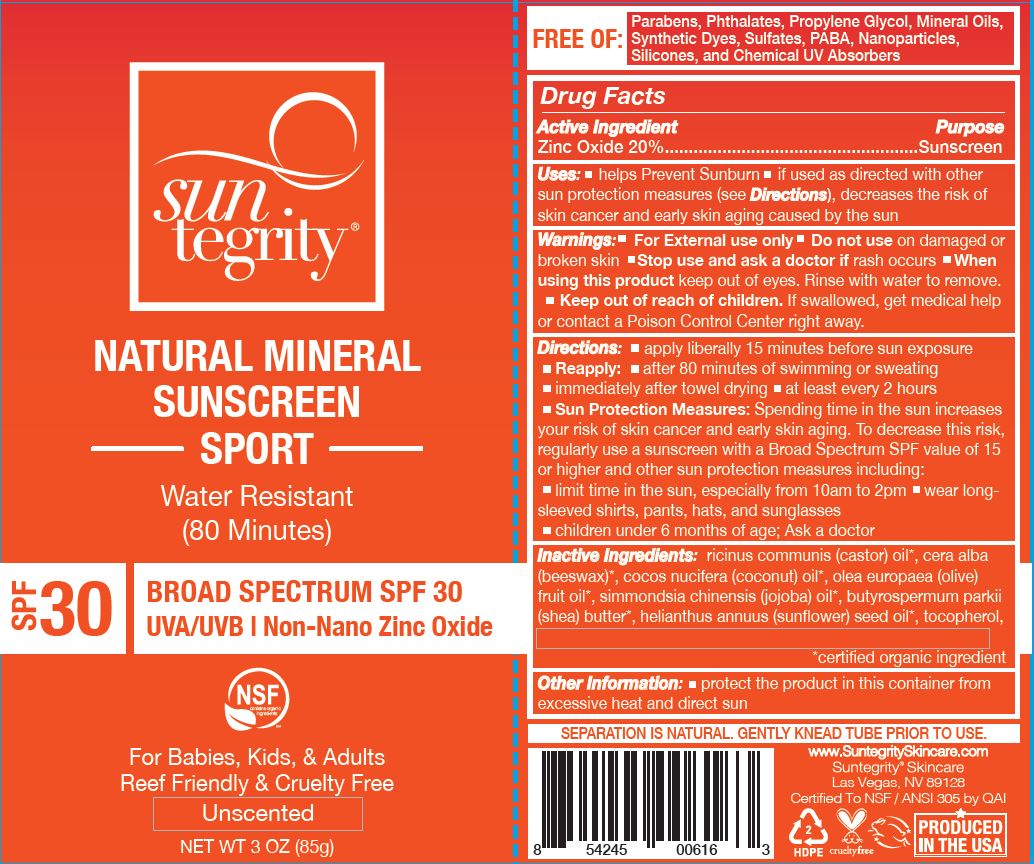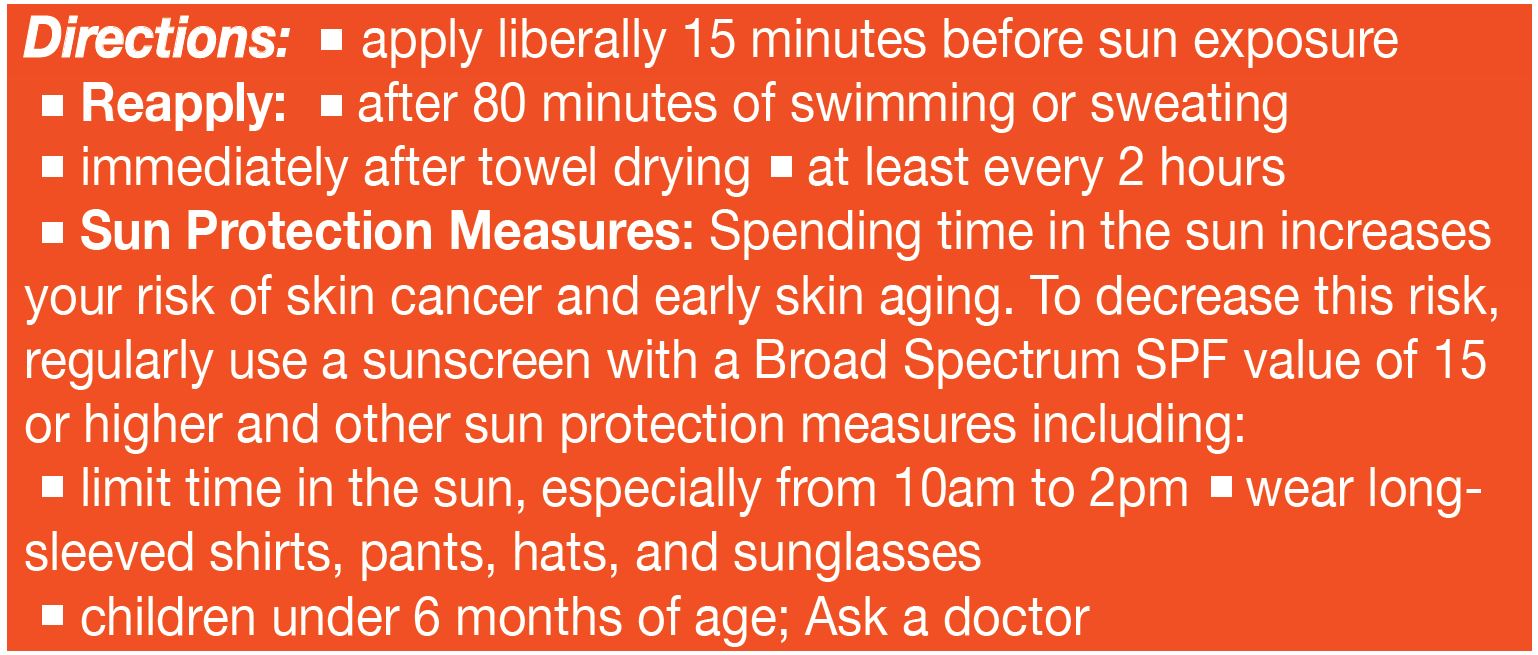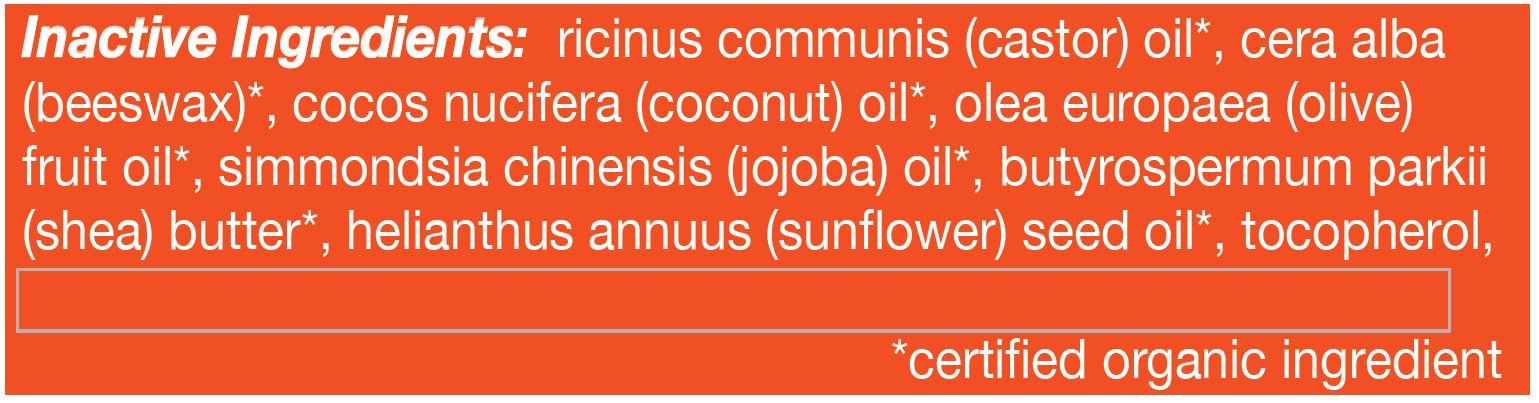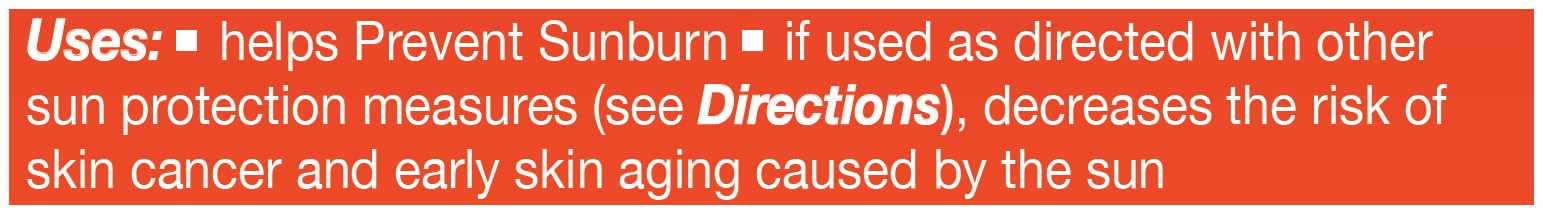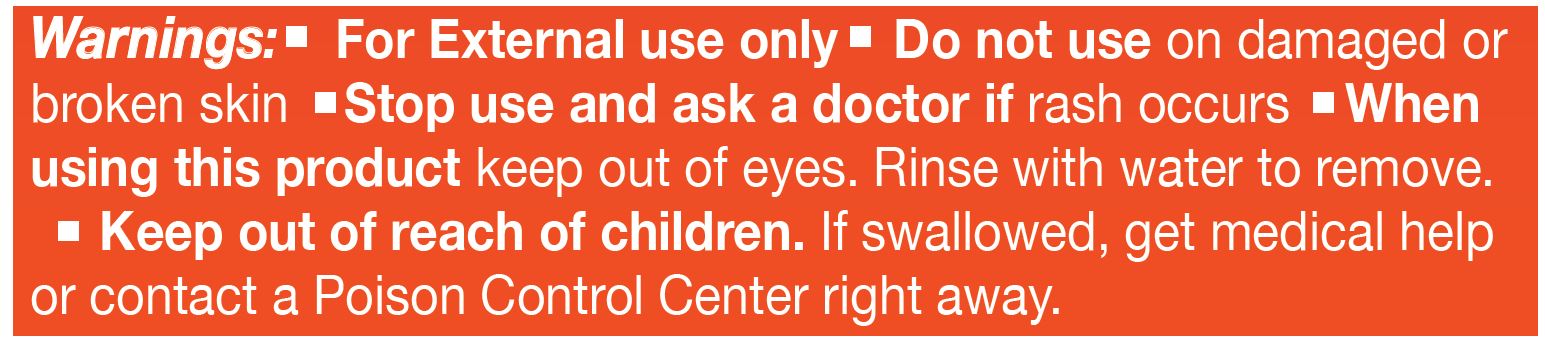 DRUG LABEL: Natural Mineral Sunscreen Sport, SPF 30  (Unscented)
NDC: 62932-257 | Form: OINTMENT
Manufacturer: Private Label Select Ltd CO
Category: otc | Type: HUMAN OTC DRUG LABEL
Date: 20211230

ACTIVE INGREDIENTS: ZINC OXIDE 20 g/100 g
INACTIVE INGREDIENTS: SUNFLOWER OIL; WHITE WAX; .GAMMA.-TOCOPHEROL; .DELTA.-TOCOPHEROL; COCONUT OIL; .ALPHA.-TOCOPHEROL, D-; OLIVE OIL; SHEA BUTTER; .BETA.-TOCOPHEROL; JOJOBA OIL; CASTOR OIL

Suntegrity, Natural Mineral Sunscreen Sport, SPF 30 (Unscented)